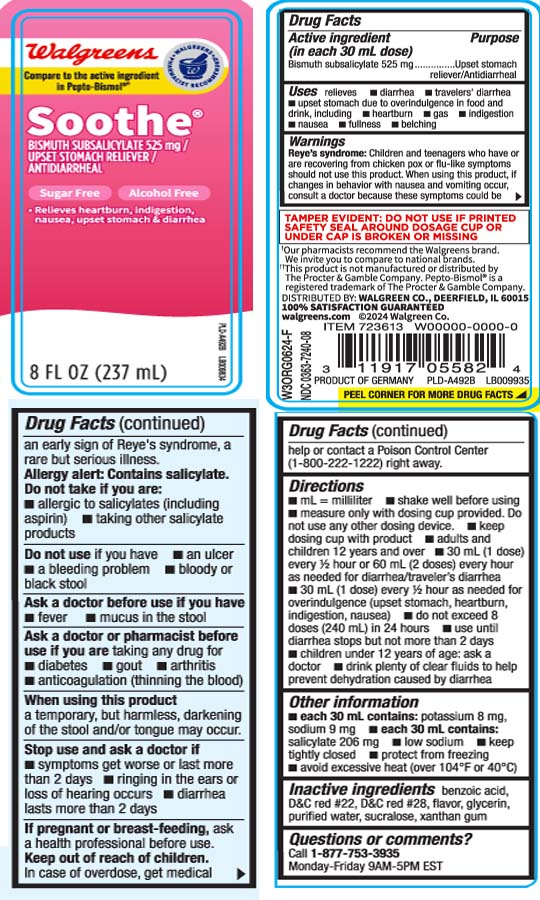 DRUG LABEL: Soothe
NDC: 0363-7240 | Form: LIQUID
Manufacturer: Walgreens
Category: otc | Type: HUMAN OTC DRUG LABEL
Date: 20251216

ACTIVE INGREDIENTS: BISMUTH SUBSALICYLATE 525 mg/30 mL
INACTIVE INGREDIENTS: BENZOIC ACID; D&C RED NO. 22; D&C RED NO. 28; GLYCERIN; WATER; XANTHAN GUM; SUCRALOSE

Drug Facts

Active ingredient (in each 30 mL dose)

Bismuth subsalicylate 525 mg

Purpose

Upset stomach reliever/Antidiarrheal

Uses

relieves

- travelers' diarrhea
- diarrhea
- upset stomach due to overindulgence in food and drink, including:
  - heartburn
  - indigestion
  - nausea
  - gas
  - fullness
  - belching

Warnings

Reye's syndrome: Children and teenagers who have or are recovering from chicken pox or flu-like symptoms should not use this product. When using this product, if changes in behavior with nausea and vomiting occur, consult a doctor because these symptoms could be an early sign of Reye's syndrome, a rare but serious illness.

Allergy alert: Contains salicylate. Do not take if you are

- allergic to salicylates (including aspirin)
- taking other salicylate products

Do not use

if you have

- an ulcer
- a bleeding problem
- bloody or black stool

Ask a doctor before use if you have

- fever
- mucus in the stool

Ask a doctor or pharmacist before use if you are

taking any drug for

- diabetes
- gout
- arthritis
- anticoagulation (thinning the blood)

When using this product

a temporary, but harmless, darkening of the stool and/or tongue may occur.

Stop use and ask a doctor if

- symptoms get worse or last more than 2 days
- ringing in the ears or loss of hearing occurs
- diarrhea lasts more than 2 days

If pregnant or breast-feeding,

ask a health professional before use.

Keep out of reach of childen.

In case of overdose, get medical help or contact a Poison Control Center (1-800-222-1222) right away.

Directions

- mL = milliliter
- shake well before using
- measure only with dosing cup provided. Do not use any other dosing device.
- keep dosing cup with product
- adults and children 12 years and over
  - 30 mL (1 dose) every 1/2 or 60 mL (2 doses) every hour as needed for diarrhea/traveler's diarrhea
  - 30 mL (1 dose) every 1/2 hour as needed for overindulgence (upset stomach, heartburn, indigestion, nausea)
  - do not exceed 8 doses (240 mL) in 24 hours
  - use until diarrhea stops but not more than 2 days
- children under 12 years of age: ask a doctor
- drink plenty of clear fluids to help prevent dehydration caused by diarrhea

Other information

- each 30 mL contains: potassium 8 mg sodium 9 mg
- each 30 mL contains: salicylate 206 mg
- low sodium
- keep tightly closed
- protect from freezing
- avoid excessive heat (over 104ºF or 40ºC)

Inactive ingredients

benzoic acid, D&C red #22, D&C red #28, flavor, glycerin, purified water, sucralose, xanthan gum

Questions or comments?

Call 1-877-753-3935 Monday-Friday 9AM-5PM EST

Principal Display Panel

Compare to the active ingredient Pepto-Bismol®††

Soothe®

BISMUTH SUBSALICYLATE 525 mg /

UPSET STOMACH RELIEVER /

ANTIDIARRHEAL

Sugar Free

Alcohol Free

- Relieves heartburn, indigestion, nausea, upset stomach & diarrhea

FL OZ (mL)

††This product is not manufactured or distributed by The Procter & Gamble Company, Pepto-Bismol® is a registered trademark of The Procter & Gamble Company.

TAMPER EVIDENT; DO NOT USE IF PRINTED SAFETY SEAL AROUND DOSAGE CUP OR UNDER CAP IS BROKEN OR MISSING.

DISTRIBUTED BY: WALGREEN CO.

DEERFIELD, IL 60015

Package Label

WALGREENS Soothe